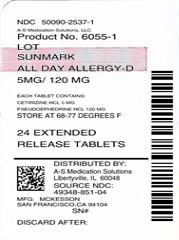 DRUG LABEL: Sunmark All Day Allergy D
NDC: 50090-2537 | Form: TABLET, EXTENDED RELEASE
Manufacturer: A-S Medication Solutions
Category: otc | Type: HUMAN OTC DRUG LABEL
Date: 20191010

ACTIVE INGREDIENTS: CETIRIZINE HYDROCHLORIDE 5 mg/1 1; PSEUDOEPHEDRINE HYDROCHLORIDE 120 mg/1 1
INACTIVE INGREDIENTS: SILICON DIOXIDE; HYPROMELLOSE, UNSPECIFIED; LACTOSE MONOHYDRATE; MAGNESIUM STEARATE; MICROCRYSTALLINE CELLULOSE; TALC; FERRIC OXIDE YELLOW

McKesson All Day Allergy-D Drug Facts

Active ingredient (in each extended release tablet)

Cetirizine HCl 5 mg

Pseudoephedrine HCl 120 mg

Purpose

Antihistamine

Nasal Decongestant

Uses

1. temporarily relieves these symptoms due to hay fever or other upper respiratory allergies:
2. runny nose
3. sneezing
4. itchy, watery eyes
5. itching of the nose or throat
6. nasal congestion
7. reduces swelling of nasal passages
8. temporarily relieves sinus congestion and pressure
9. temporarily restores freer breathing through the nose

Warnings

Do not use

1. if you have ever had an allergic reaction to this product or any of its ingredients or to an antihistamine containing hydroxyzine.
2. if you are now taking a prescription monoamine oxidase inhibitor (MAOI) (certain drugs for depression, psychiatric, or emotional conditions, or Parkinson’s disease), or for 2 weeks after stopping the MAOI drug. If you do not know if your prescription drug contains an MAOI, ask a doctor or pharmacist before taking this product.

Ask a doctor before use if you have

1. heart disease
2. thyroid disease
3. diabetes
4. glaucoma
5. high blood pressure
6. trouble urinating due to an enlarged prostate gland
7. liver or kidney disease. Your doctor should determine if you need a different dose.

Ask a doctor or pharmacist before use if you are

taking tranquilizers or sedatives.

When using this product

1. do not use more than directed
2. drowsiness may occur
3. avoid alcoholic drinks
4. alcohol, sedatives, and tranquilizers may increase drowsiness
5. be careful when driving a motor vehicle or operating machinery

Stop use and ask a doctor if

1. an allergic reaction to this product occurs. Seek medical help right away.
2. you get nervous, dizzy, or sleepless
3. symptoms do not improve within 7 days or are accompanied by fever

If pregnant or breast-feeding:

1. if breast-feeding: not recommended
2. if pregnant: ask a health professional before use.

Keep out of reach of children.

In case of overdose, get medical help or contact a Poison Control Center right away.

Directions

1. do not break or chew tablet; swallow tablet whole

adults and children 12 years and over | take 1 tablet every 12 hours; do not take more than 2 tablets in 24 hours.
adults 65 years and over | ask a doctor
children under 12 years of age | ask a doctor
consumers with liver or kidney disease | ask a doctor

Other information

1. store between 20° to 25°C (68° to 77°F)

Inactive ingredients

colloidal silicon dioxide, hydroxypropyl cellulose, hypromellose, lactose monohydrate, magnesium stearate, microcrystalline cellulose, talc, yellow iron oxide

Questions or comments?

1-800-719-9260

HOW SUPPLIED

Product: 50090-2537

NDC: 50090-2537-1 6 TABLET, EXTENDED RELEASE in a BLISTER PACK / 4 in a CARTON